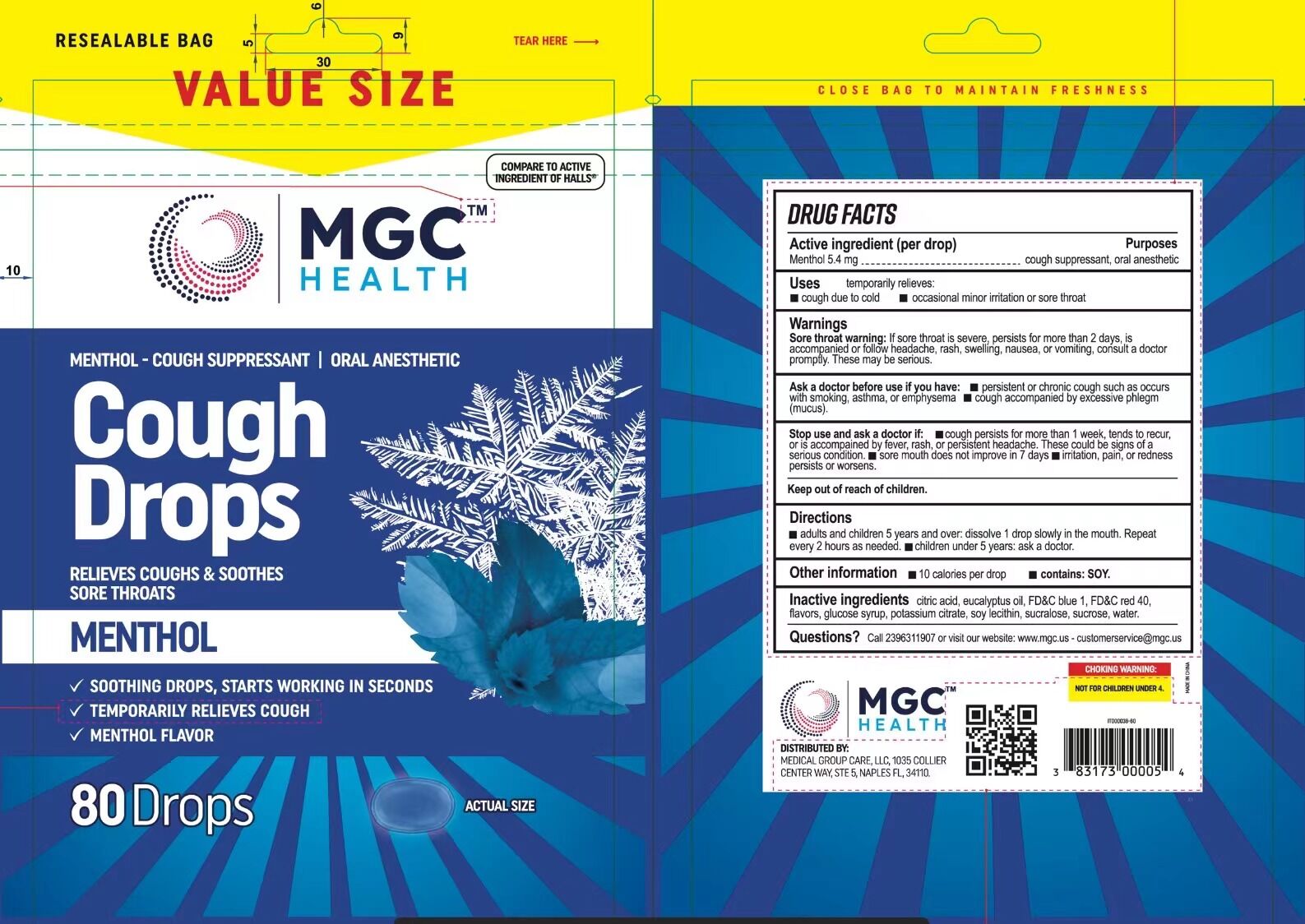 DRUG LABEL: Cough Drops
NDC: 84236-101 | Form: TABLET, ORALLY DISINTEGRATING
Manufacturer: Xiamen Misero Biotechnology Co, Ltd
Category: otc | Type: HUMAN OTC DRUG LABEL
Date: 20240730

ACTIVE INGREDIENTS: MENTHOL 5.4 mg/1 1
INACTIVE INGREDIENTS: SUCRALOSE; CITRIC ACID MONOHYDRATE; FD&C BLUE NO. 1; SUCROSE; CORN SYRUP; SOYBEAN LECITHIN; POTASSIUM CITRATE; EUCALYPTUS OIL; FD&C RED NO. 40; WATER

Cough Drops

Cough Drops

ACTIVE INGREDIENT

MENTHOL 0.18%

PURPOSE

cough suppressant, oral anesthetic

INDICATIONS AND USAGE

temporarily relieves:
cough due to cold
occasiona! minor irritation or sore throat

WARNINGS

Sore throat warninq: lf sore throat is severe, persists for more than 2 days, isaccompanied or follow headache, rash, swelling, nausea, or vomiting, consult a doctorpromptly. These may be serious.

Ask a doctor before use if you have:
persistent or chronic cough such as occurs with smoking, asthma, or emphysema.
cough accompanied by excessive phlegm (mucus).

Ask a doctor before use if you have:
persistent or chronic cough such as occurs with smoking, asthma, or emphysema.
cough accompanied by excessive phlegm (mucus).

STOP USE

cough persists for more than 1 week, tends to recur,or is accompained by tever, rash, or persistent headache. These could be sions of a serious condition.
sore mouth does not improve in 7 days.
irritation, pain, or redness persists or worsens.

Keep out of reach of children.

DOSAGE AND ADMINISTRATION

adults and children 5 years and over: dissolve 1 drop slowly in the mouth. Repeat every 2 hours as needed.
children under 5 years: ask a doctor.

STORAGE AND HANDLING

Store in a cool place.

INACTIVE INGREDIENT

EUCALYPTUS OIL
FD&C BLUE NO. 1
FD&C RED NO. 40
POTASSIUM CITRATE
SOY LECITHIN
SUCRALOSE
SUCROSE
GLUCOSE SYRUP
CITRIC ACID
Water